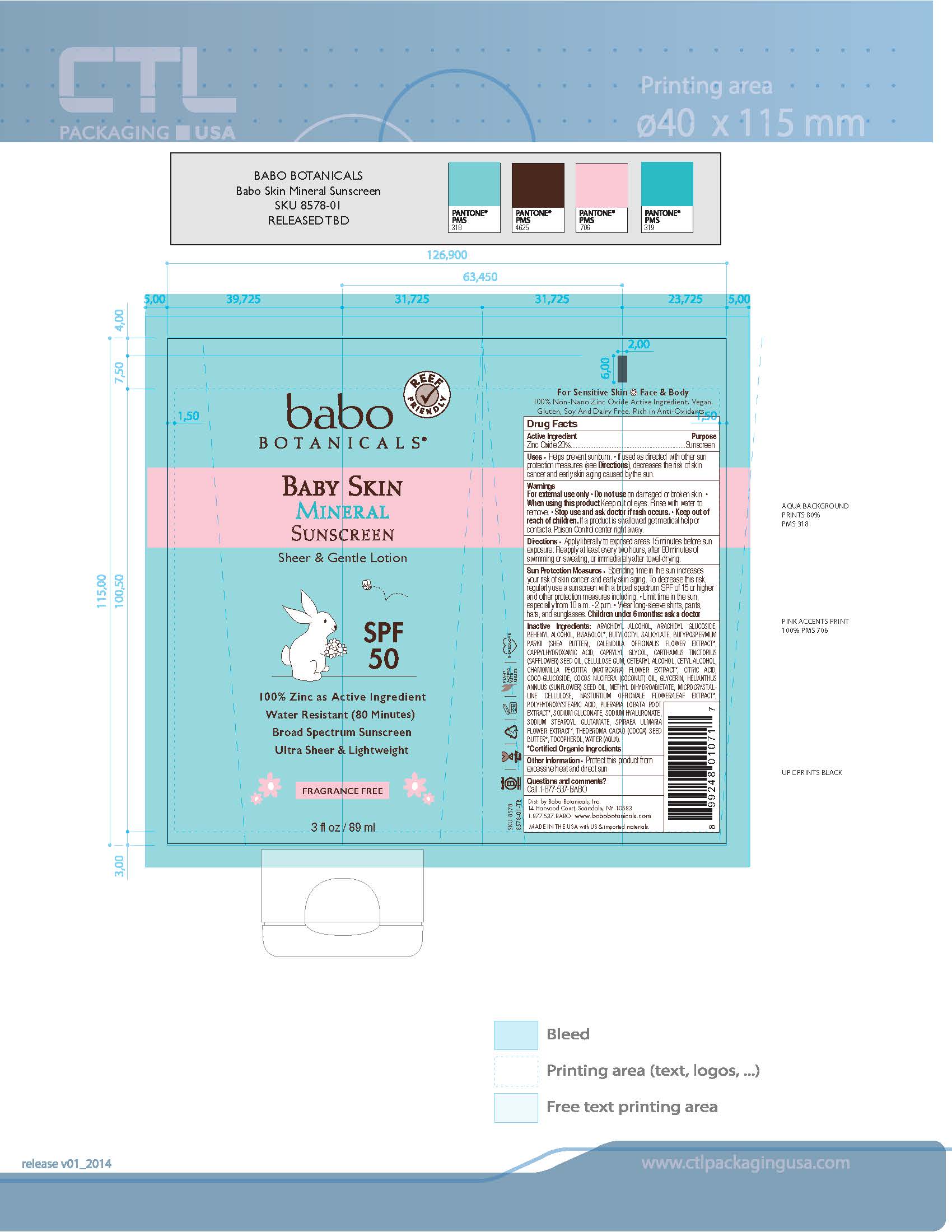 DRUG LABEL: Baby Skin Mineral Sunscreen
NDC: 79265-8578 | Form: LOTION
Manufacturer: Babo Botanicals, Inc.
Category: otc | Type: HUMAN OTC DRUG LABEL
Date: 20241212

ACTIVE INGREDIENTS: ZINC OXIDE 20 g/100 mL
INACTIVE INGREDIENTS: CALENDULA OFFICINALIS FLOWER 0.0001 mL/100 mL; PUERARIA MONTANA VAR. LOBATA ROOT 0.0001 mL/100 mL; CETOSTEARYL ALCOHOL 1.3 mL/100 mL; HYALURONATE SODIUM 0.2 mL/100 mL; SODIUM STEAROYL GLUTAMATE 1.3 mL/100 mL; TOCOPHEROL 0.75 mL/100 mL; LEVOMENOL 0.3 mL/100 mL; GLYCERIN 0.15 mL/100 mL; WATER 46.0495 mL/100 mL; NASTURTIUM OFFICINALE FLOWERING TOP 0.0001 mL/100 mL; POLYHYDROXYSTEARIC ACID (2300 MW) 0.25 mL/100 mL; SODIUM GLUCONATE 0.2 mL/100 mL; CETYL ALCOHOL 0.75 mL/100 mL; CITRIC ACID MONOHYDRATE 0.2 mL/100 mL; CAPRYLYL GLYCOL 0.7 mL/100 mL; CARBOXYMETHYLCELLULOSE SODIUM, UNSPECIFIED FORM 0.144 mL/100 mL; CHAMOMILE 0.0001 mL/100 mL; BUTYLOCTYL SALICYLATE 5 mL/100 mL; ARACHIDYL ALCOHOL 0.972 mL/100 mL; ARACHIDYL GLUCOSIDE 0.324 mL/100 mL; DOCOSANOL 0.504 mL/100 mL; SHEA BUTTER 2.1 mL/100 mL; CAPRYLHYDROXAMIC ACID 0.15 mL/100 mL; METHYL DIHYDROABIETATE 3 mL/100 mL; COCO GLUCOSIDE 0.7 mL/100 mL; COCONUT OIL 5 mL/100 mL; SUNFLOWER OIL 5.1 mL/100 mL; MICROCRYSTALLINE CELLULOSE 1.056 mL/100 mL; FILIPENDULA ULMARIA FLOWER 0.0001 mL/100 mL; COCOA BUTTER 0.8 mL/100 mL; SAFFLOWER OIL 3 mL/100 mL

8578 SPF 50 Baby Skin Mineral Sunscreen Lotion

This is a sunscreen with the approved active ingredient of Zinc Oxide at 20%.

Active Ingredient(s)

Zinc Oxide 20%. Purpose: Sunscreen

Purpose

Sunscree

Use

Helps prevent sunburn. • If used as directed with other sun protection measures (see Directions), decreases the risk of skin cancer and early skin aging caused by the sun.

Warnings

For external use only.

Do not use on damaged or broken skin. • When using this product Keep out of eyes. Rinse with water to remove. • Stop use and ask doctor if rash occurs. • Keep out of reach of children. If a product is swallowed get medical help or contact a Poison Control center right away.

Directions

Apply liberally to exposed areas 15 minutes before sun exposure. Reapply at least every two hours, after 80 minutes of swimming or sweating, or immediately after towel-drying.

Other information

Protect this product from excessive heat and direct sun

Inactive ingredients

ARACHIDYL ALCOHOL, ARACHIDYL GLUCOSIDE, BEHENYL ALCOHOL, BISABOLOL*, BUTYLOCTYL SALICYLATE, BUTYROSPERMUM PARKII (SHEA BUTTER), CALENDULA OFFICINALIS FLOWER EXTRACT*, CAPRYLHYDROXAMIC ACID, CAPRYLYL GLYCOL, CARTHAMUS TINCTORIUS (SAFFLOWER) SEED OIL, CELLULOSE GUM, CETEARYL ALCOHOL, CETYL ALCOHOL, CHAMOMILLA RECUTITA (MATRICARIA) FLOWER EXTRACT*, CITRIC ACID, COCO-GLUCOSIDE, COCOS NUCIFERA (COCONUT) OIL, GLYCERIN, HELIANTHUS ANNUUS (SUNFLOWER) SEED OIL, METHYL DIHYDROABIETATE, MICROCRYSTAL-LINE CELLULOSE, NASTURTIUM OFFICINALE FLOWER/LEAF EXTRACT*, POLYHYDROXYSTEARIC ACID, PUERARIA LOBATA ROOT EXTRACT*, SODIUM GLUCONATE, SODIUM HYALURONATE, SODIUM STEAROYL GLUTAMATE, SPIRAEA ULMARIA FLOWER EXTRACT*, THEOBROMA CACAO (COCOA) SEED BUTTER*, TOCOPHEROL, WATER (AQUA).*Certified Organic Ingredients

Package Label - Principal Display Panel

3 fl oz / 89 mL ml NDC: 79265-8578-3